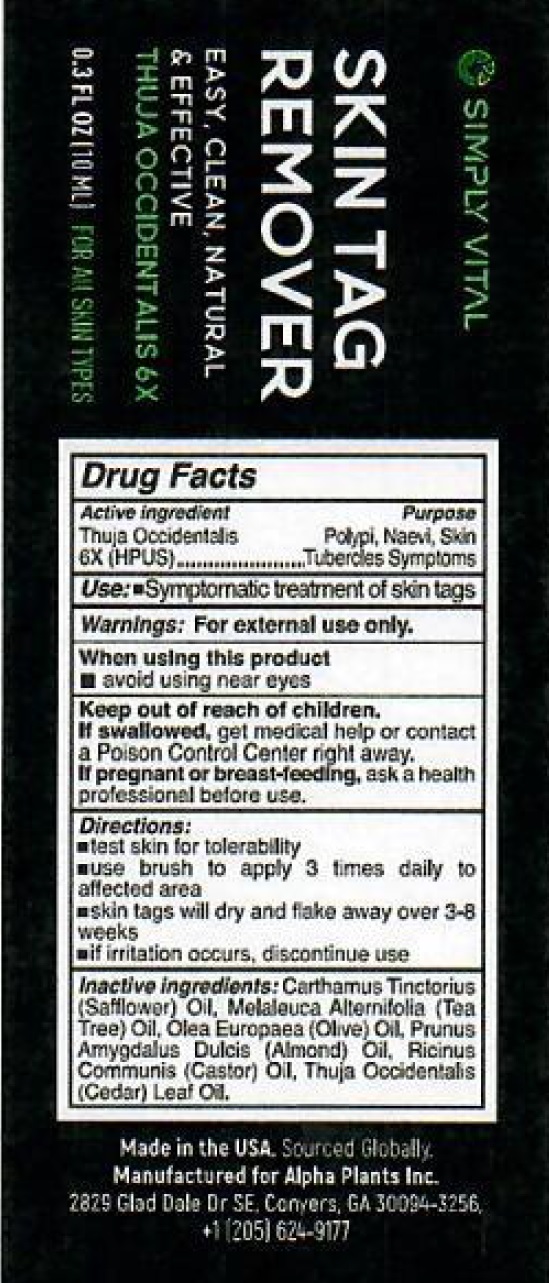 DRUG LABEL: SIMPLY VITAL Skin Tag Remover
NDC: 82460-343 | Form: SOLUTION
Manufacturer: ALPHA PLANTS INC
Category: homeopathic | Type: HUMAN OTC DRUG LABEL
Date: 20220720

ACTIVE INGREDIENTS: THUJA OCCIDENTALIS LEAFY TWIG 6 [hp_X]/1 mL
INACTIVE INGREDIENTS: SAFFLOWER; TEA TREE OIL; OLIVE OIL; ALMOND; CASTOR OIL

SIMPLY VITAL Skin Tag Remover

Active ingredient

Thuja Occidentalis 6X (HPUS)

Purpose

Polypi, Naevi, Skin Tubercles Symptoms

Use:

- Symptomatic treatment of skin tags

Warnings:

For external use only.

When using this product

- avoid using near eyes

Keep out of reach of children.

If swallowed, get medical help or contact a Poison Control Center right away.

If pregnant or breast-feeding,

ask a health professional before use.

Directions:

- test skin for tolerabillity
- use brush to apply 3 times daily to affected area
- skin tags will dry and flake away over 3-8 weeks
- if irritation occurs, discontinue use

Inactive ingredients:

Carthamus Tinctorius (Safflower) Oil, Melaleuca Alternifolia (Tea Tree) Oil, Olea Europaea (Olive) Oil, Prunus Amygdalus Dulcis (Almond) Oil, Ricinus Communis (Castor) Oil, Thuja Occidentalis (Cedar) Leaf Oil.